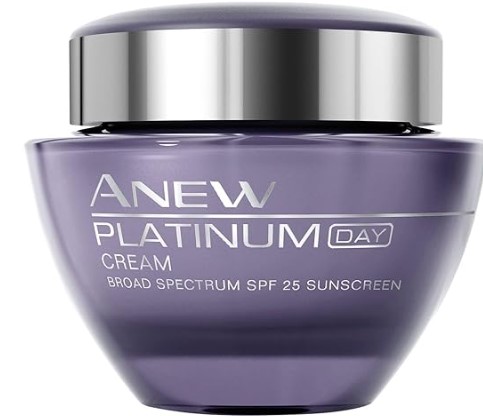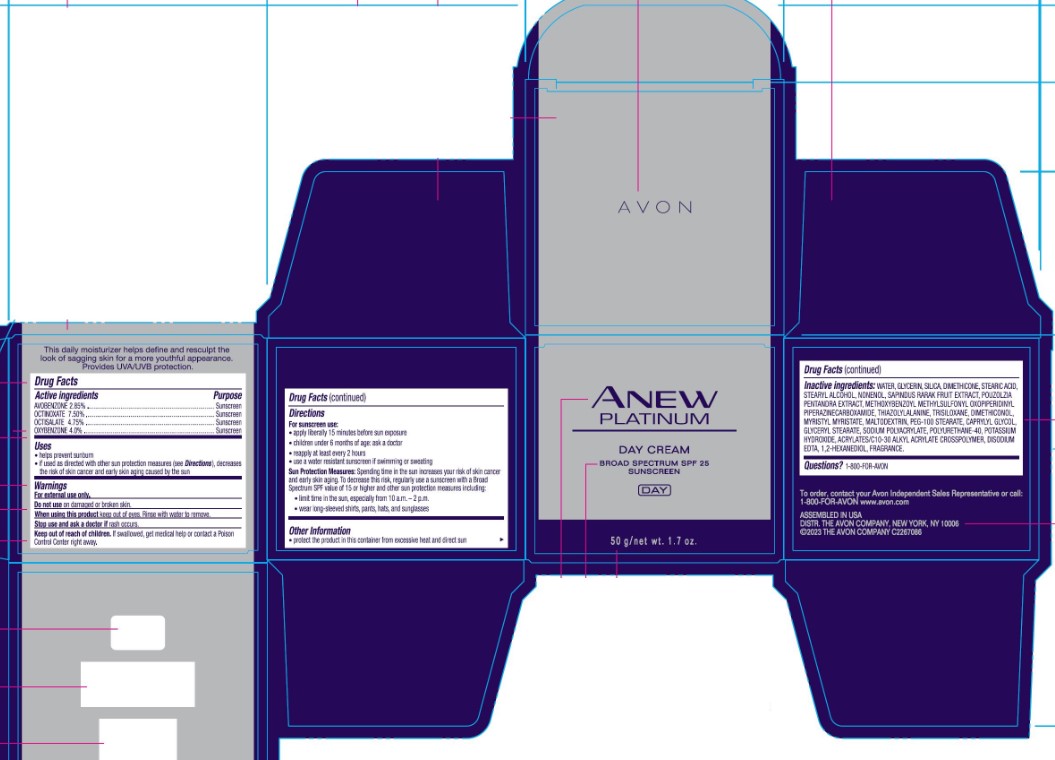 DRUG LABEL: Anew Platinum DayCream Broad Spectrum SPF 25
NDC: 68577-170 | Form: CREAM
Manufacturer: COSMAX USA, CORPORATION
Category: otc | Type: HUMAN OTC DRUG LABEL
Date: 20241219

ACTIVE INGREDIENTS: OXYBENZONE 4 mg/1 g; OCTINOXATE 7.5 mg/1 g; OCTISALATE 4.75 mg/1 g; AVOBENZONE 2.85 mg/1 g
INACTIVE INGREDIENTS: PEG-100 STEARATE; THIAZOLYLALANINE; TRISILOXANE; ACRYLATES/C10-30 ALKYL ACRYLATE CROSSPOLYMER (60000 MPA.S); SODIUM POLYACRYLATE (8000 MW); STEARYL ALCOHOL; NONENOL; GLYCERYL STEARATE; EDETATE DISODIUM; WATER; DIMETHICONE; DIMETHICONOL (2000 CST); MALTODEXTRIN; STEARIC ACID; SAPINDUS RARAK FRUIT; 1,2-HEXANEDIOL; MYRISTYL MYRISTATE; GLYCERIN; SILICA; CAPRYLYL GLYCOL; POTASSIUM HYDROXIDE

AVON ANEW PLATINUM DAY CREAM BROAD SPECTRUM SPF 25 SUNSCREEN

Active Ingredients

OCTINOXATE 7.5%

OCTISALATE 4.8%

OXYBENZONE 4%

AVOBENZONE 2.9%

Purpose

Sunscreen

USES

- helps prevent sunburn
- if used as directed with other sun protection measures (see Directions), decreases the risk of skin cancer and skin aging caused by the sun

Warnings

For external use only

Do not use on damaged broken skin

When using this product keep out of eyes. Rinse with water to remove

Stop use and ask a doctor if rash occurs.

Keep out of reach of children. If swallowed, get medical help or contact a Poison Control Center right away.

DIRECTIONS

- apply liberally 15 minutes before sun exposure
- children less than 6 months of age: ask a doctor
- reapply at least every 2 hours
- use a water resistant sunscreen if swimming or sweating

Sun Protection Measures: Spending time in the sun increases your risk of skin cancer and early skin aging. To decrease this risk, regularly use a sunscreen with a Broad Spectrum SPF value of 15 or higher and other sun protection measures including:

- limit time in the sun, especially from 10 a.m. – 2 p.m.
- wear long-sleeved shirts, pants, hats, and sunglasses

OTHER INFORMATION

• protect the product in this container from excessive heat and direct sun

• the product may stain certain types of fabrics

Inactive Ingredients:

WATER, GLYCERIN, SILICA, DIMETHICONE, STEARIC ACID, STEARYL ALCOHOL, NONENOL, SAPINDUS RARAK FRUIT EXTRACT, POUZOLZIA PENTANDRA EXTRACT, METHOXYBENZOYL METHYLSULFONYL OXOPIPERIDINYL PIPERAZINECARBOXAMIDE, THIAZOLYLALANINE, TRISILOXANE, DIMETHICONOL, MYRISTYL MYRISTATE, MALTODEXTRIN, PEG-100 STEARATE, CAPRYLYL GLYCOL, GLYCERYL STEARATE, SODIUM POLYACRYLATE, POLYURETHANE-40, POTASSIUM HYDROXIDE, ACRYLATES/C10-30 ALKYL ACRYLATE CROSSPOLYMER, DISODIUM EDTA, 1,2-HEXANEDIOL, FRAGRANCE